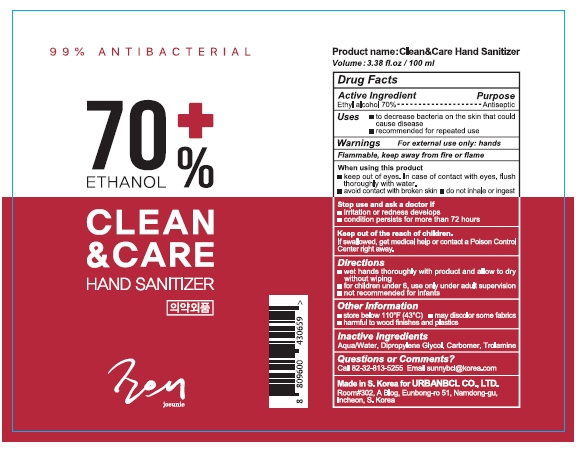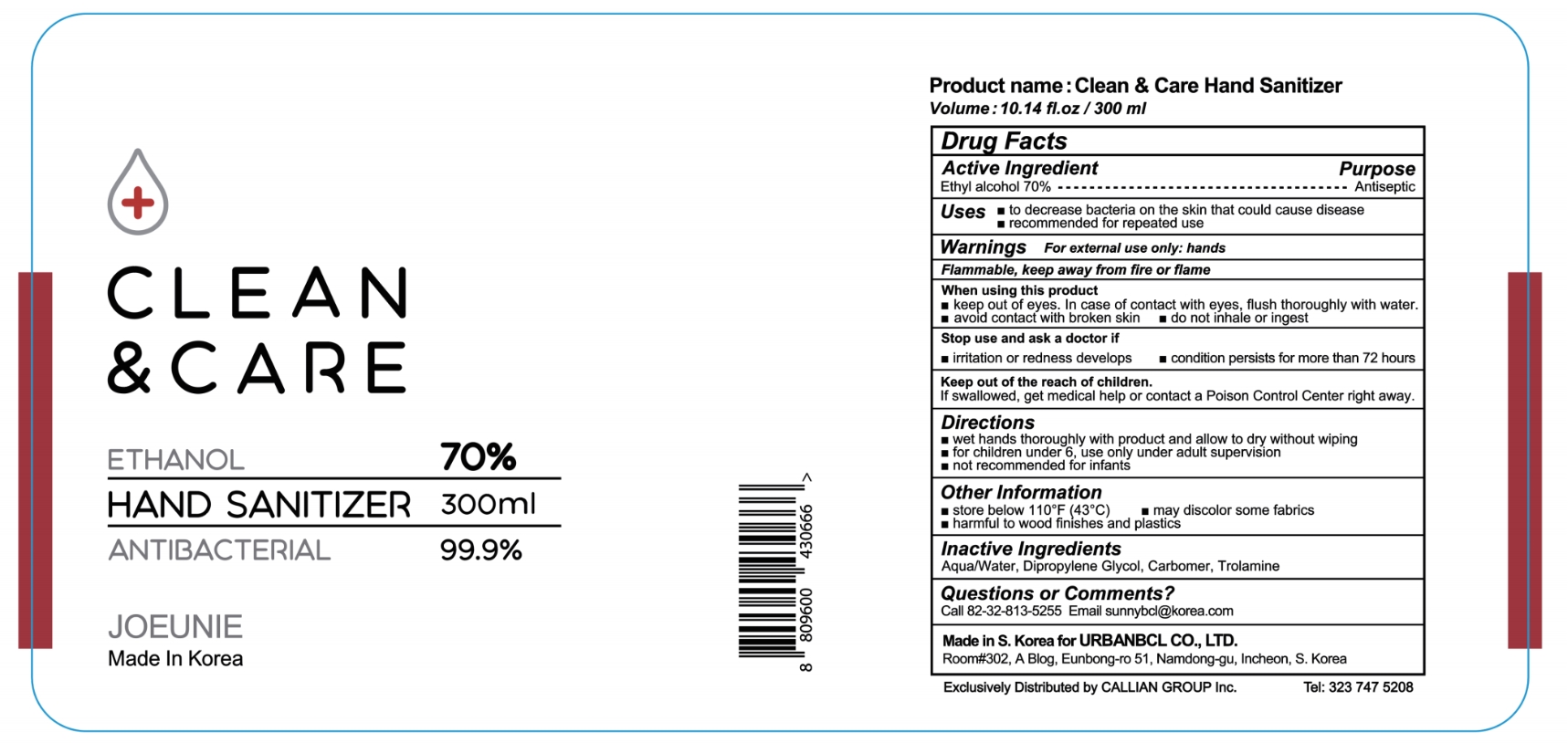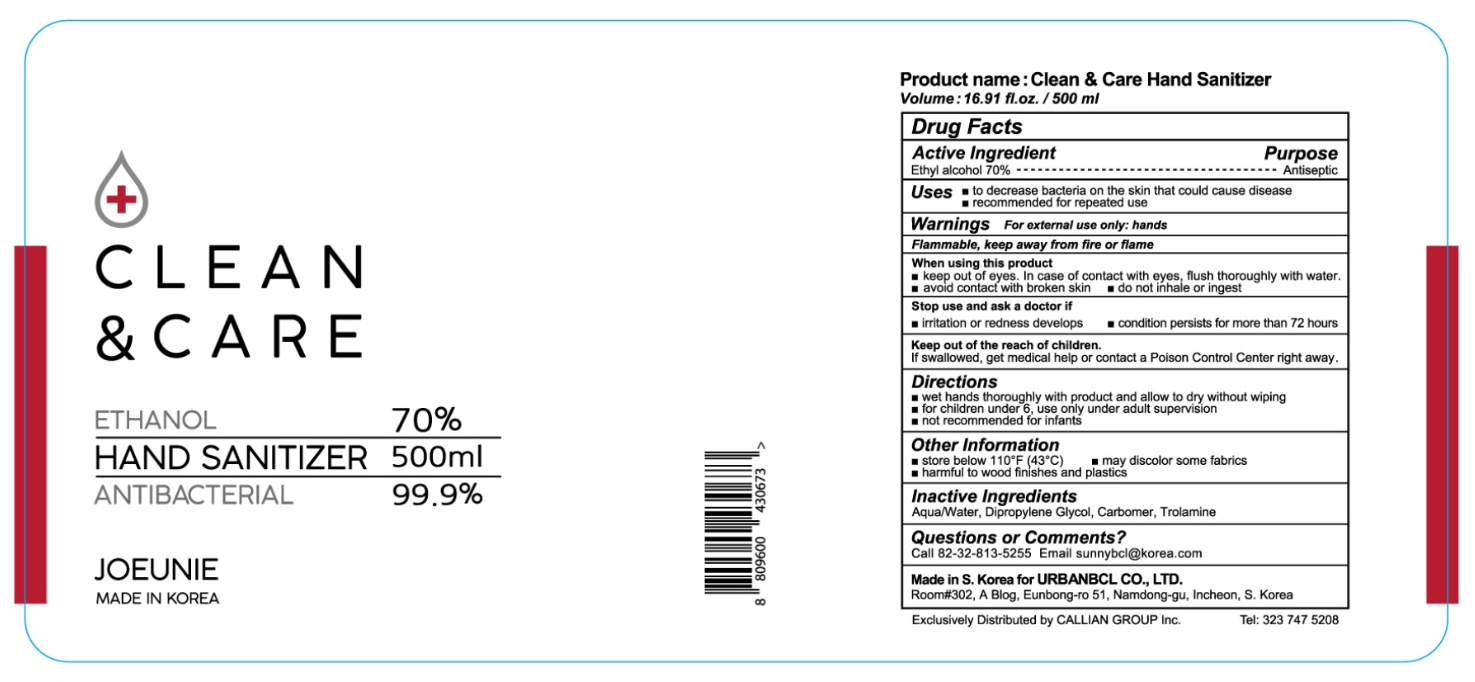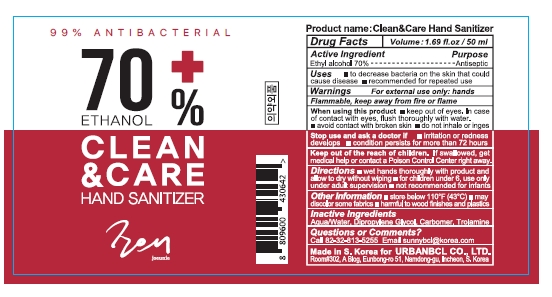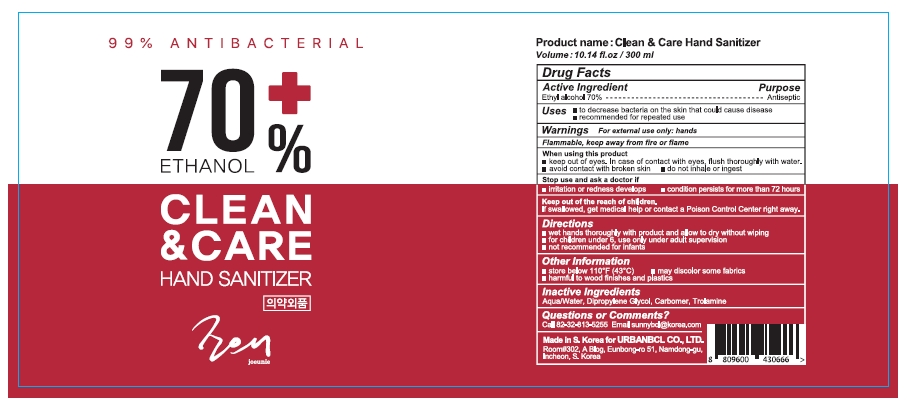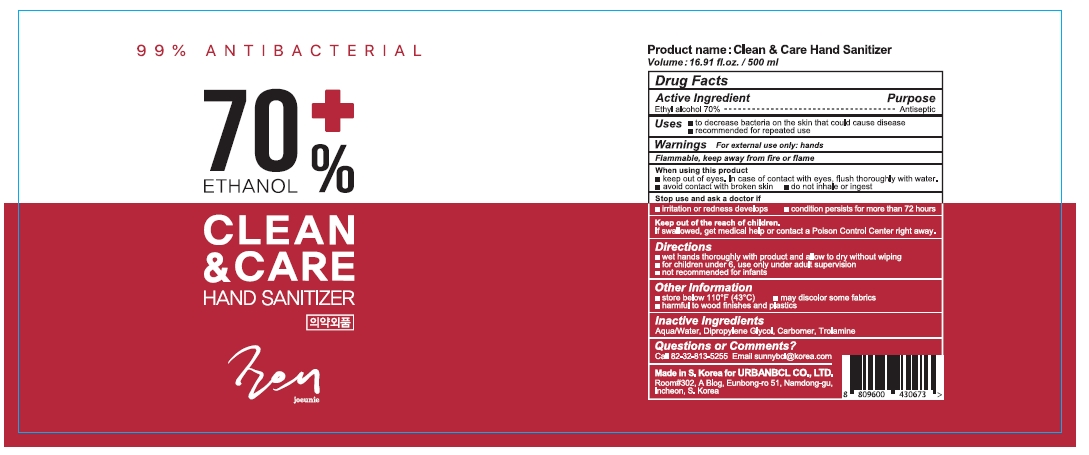 DRUG LABEL: Clean and Care Hand Sanitizer
NDC: 74633-102 | Form: GEL
Manufacturer: JOEUNIE
Category: otc | Type: HUMAN OTC DRUG LABEL
Date: 20200522

ACTIVE INGREDIENTS: ALCOHOL 210 g/300 mL
INACTIVE INGREDIENTS: TROLAMINE; DIPROPYLENE GLYCOL; WATER; CARBOMER HOMOPOLYMER, UNSPECIFIED TYPE

Clean & Care Hand Sanitizer

Active ingredient

Alcohol (70%)

Uses

Hand sanitizer for decreasing bacteria on skin

Purpose

Antibacterial

Warnings

For external use only

Do not use if you are allergic to any of the ingredients

When using this product avoid contact with eyes. If contact occurs, rinse eyes thoroughly with water. avoid contact with broken, irritated, or itching skin. Do not puncture or incinerate.

Stop use and ask a doctor if irritation or redness develops and condition persists for more than 72 hours

If pregnant or breast-feeding, ask a health professional before use.

Directions

Take appropriate amount onto your hand and spread it all the way to fingertips. Rub the contents until it dries

Inactive ingredients

Carbomer, Trolamine, Dipropylene Glycol, Water

Keep out of reach of children. If swallowed, get medical help or contact a Poison Control Center (1-800-222-1222) right away.